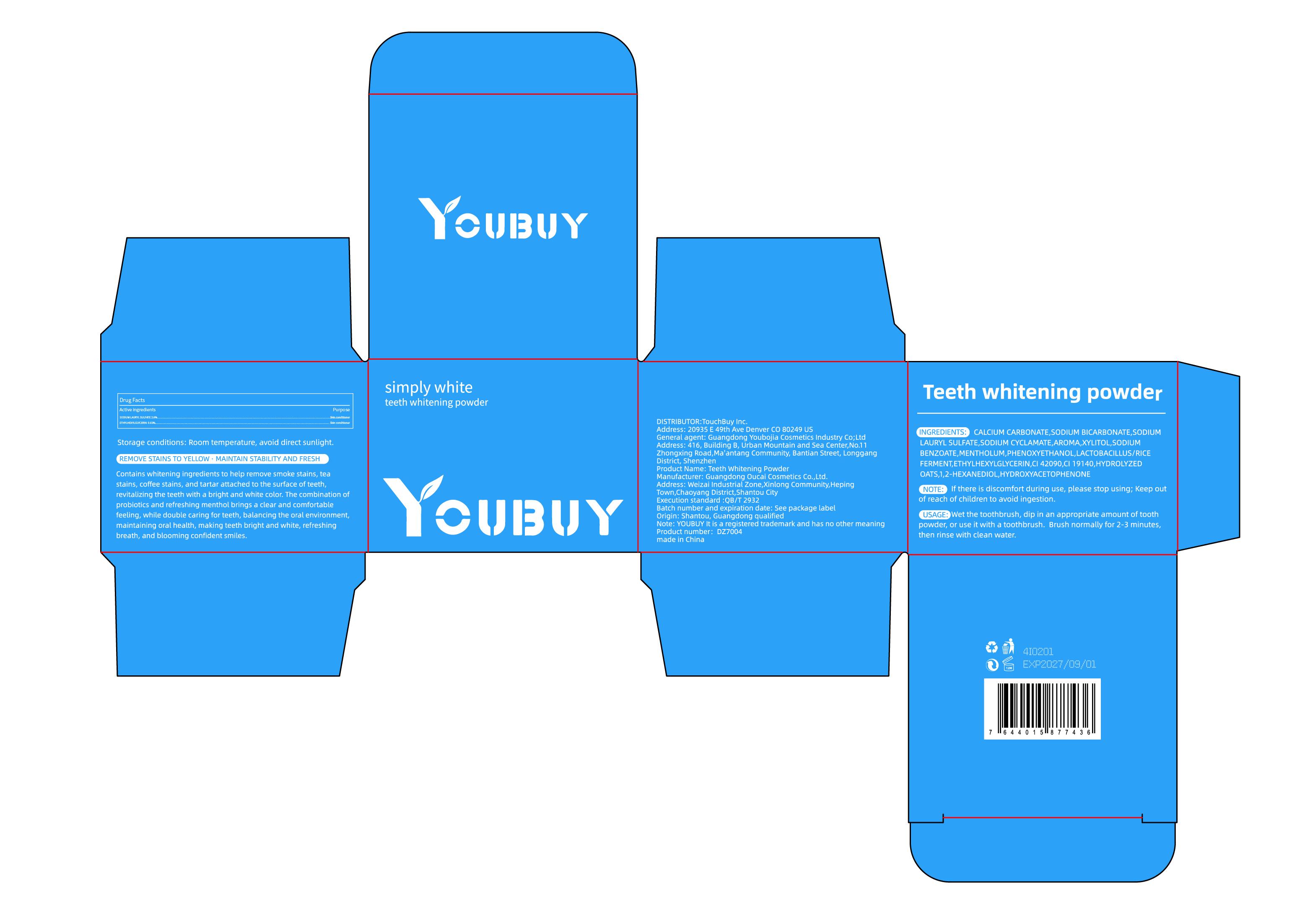 DRUG LABEL: YOUBUY Teeth whitening powder
NDC: 84712-014 | Form: POWDER
Manufacturer: Guangdong Youbaijia Cosmetic Industry Co., Ltd
Category: otc | Type: HUMAN OTC DRUG LABEL
Date: 20240914

ACTIVE INGREDIENTS: SODIUM LAURYL SULFATE 0.39 g/15 g; ETHYLHEXYLGLYCERIN 0.003 g/15 g
INACTIVE INGREDIENTS: SODIUM BICARBONATE 5.25 g/15 g; CALCIUM CARBONATE 8.7945 g/15 g

ACTIVE INGREDIENT

SODIUM LAURYL SULFATE 2.6%
ETHYLHEXYLGLYCERIN 0.02%

INACTIVE INGREDIENT

CALCIUM CARBONATE

SODIUM BICARBONATE

SODIUM CYCLAMATE

AROMA,XYLITOL

SODIUM BENZOATE

MENTHOLUM

PHENOXYETHANOL

LACTOBACILLUS/RICE FERMENT

CI 42090

CI 19140

HYDROLYZED OATS

1,2-HEXANEDIOL

HYDROXYACETOPHENONE

Do not use on damaged skin.

Keep away from children. Do not swallow.

PURPOSE

REMOVE STAINS TO YELLOW , MAINTAIN STABILITY AND FRESH

QUESTIONS

Contact name: Jessie Peng
Company phone number: +1 818 579 7288
Company e-mail: jessie@registeragentllc.com

STOP USE

If there is discomfort during use, please stop using

WHEN USING

keep out of eyes. Rinse with water to remove.

STORAGE AND HANDLING

Keep away from light and in a dry place.

WARNINGS

For external use only.

INDICATIONS AND USAGE

Contains whitening ingredients to help remove smoke stains, tea stains, coffee stains, and tartar attached to the surface of teeth,revitalizing the teeth with a bright and white color. The combination of probiotics and refreshing menthol brings a clear and comfortable feeling, while double caring for teeth, balancing the oral environment,maintaining oral health, making teeth bright and white, refreshing breath, and blooming confident smiles.

DOSAGE AND ADMINISTRATION

USAGE:Wet the toothbrush, dip in an appropriate amount of tooth powder, or use it with a toothbrush. Brush normally for 2-3 minutes, then rinse with clean water.